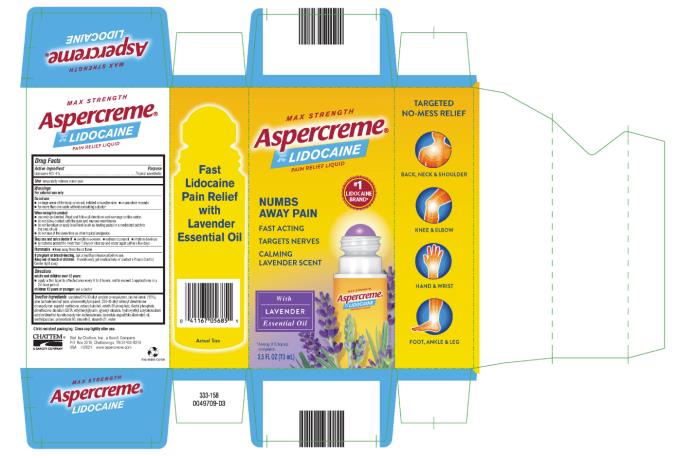 DRUG LABEL: Aspercreme Lidocaine No-Mess plus Lavender
NDC: 41167-0568 | Form: LIQUID
Manufacturer: Chattem, Inc.
Category: otc | Type: HUMAN OTC DRUG LABEL
Date: 20231025

ACTIVE INGREDIENTS: LIDOCAINE HYDROCHLORIDE 4 g/100 mL
INACTIVE INGREDIENTS: CARBOMER INTERPOLYMER TYPE A (55000 CPS); ALCOHOL; ALOE VERA LEAF; AMINOMETHYLPROPANOL; CAPRYLYL TRISILOXANE; CETOSTEARYL ALCOHOL; CETETH-20 PHOSPHATE; DIHEXADECYL PHOSPHATE; DIMETHICONE; EDETATE DISODIUM ANHYDROUS; ETHYLHEXYLGLYCERIN; GLYCERYL MONOSTEARATE; HYDROXYETHYL ACRYLATE/SODIUM ACRYLOYLDIMETHYL TAURATE COPOLYMER (100000 MPA.S AT 1.5%); ISOHEXADECANE; LAVENDER OIL; METHYLPARABEN; POLYSORBATE 60; STEARETH-2; STEARETH-21

Aspercreme with Lidocaine No-Mess Lavender

ASPERCREME LIDOCAINE WITH LAVENDER NO-MESS

Drug Facts

Active ingredient

Lidocaine HCl 4%

Purpose

Topical anesthetic

Use

temporarily relieves minor pain

Warnings

For external use only

Do not use

■ on large areas of the body or on cut, irritated or swollen skin

■ on puncture wounds

■ for more than one week without consulting a doctor

When using this product

■ use only as directed. Read and follow all directions and warnings on this carton.

■ do not allow contact with the eyes and mucous membranes

■ do not bandage or apply local heat (such as heating pads) or a medicated patch to the area of use

■ do not use at the same time as other topical analgesics

Stop use and ask a doctor if

■ condition worsens

■ redness is present

■ irritation develops

■ symptoms persist for more than 7 days or clear up and occur again within a few days

Flammable ■ Keep away from fire or flame

If pregnant or breast-feeding,

ask a health professional before use.

Keep out of reach of children.

If swallowed, get medical help or contact a Poison Control Center right away.

Directions

adults and children over 12 years:

■ apply a thin layer to affected area every 6 to 8 hours, not to exceed 3 applications in a 24 hour period

children 12 years or younger: ask a doctor

Inactive ingredients

acrylates/C10-30 alkyl acrylate crosspolymer, alcohol denat. (15%), aloe barbadensis leaf juice, aminomethyl propanol, C30-45 alkyl cetearyl dimethicone crosspolymer, caprylyl methicone, cetearyl alcohol, ceteth-20 phosphate, dicetyl phosphate, dimethicone, disodium EDTA, ethylhexylglycerin, glyceryl stearate, hydroxyethyl acrylate/sodium acryloyldimethyl taurate copolymer, isohexadecane, lavandula angustifolia (lavender) oil, methylparaben, polysorbate 60, steareth-2, steareth-21, water

Child-resistant packaging. Close cap tightly after use.

Keep carton as it contains important information.

PRINCIPAL DISPLAY PANEL

MAX STRENGTH
Aspercreme
with 4% LIDOCAINE
PAIN RELIEF LIQUID
With LAVENDER Essential Oil
2.5 FL OZ (73 mL)